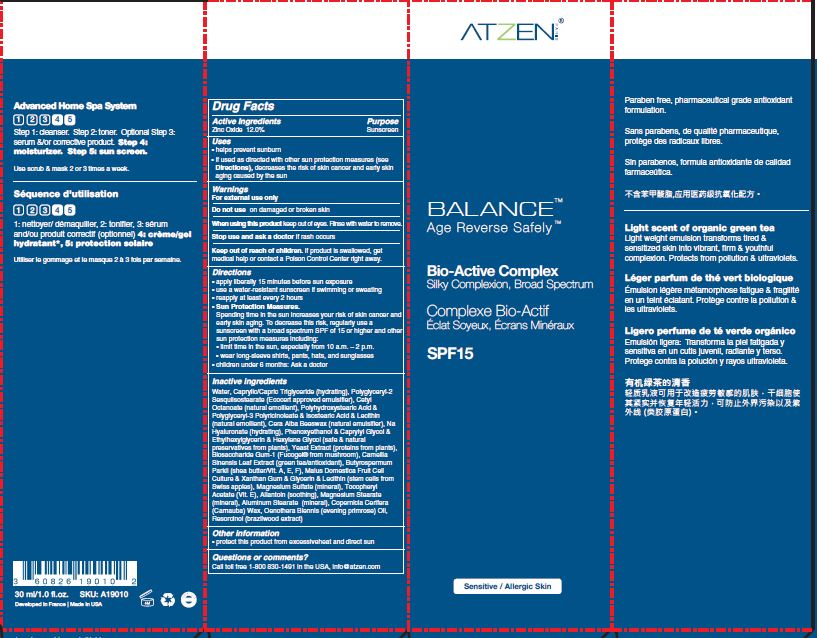 DRUG LABEL: Bio Active Complex SPF 15
NDC: 62742-4163 | Form: CREAM
Manufacturer: ALLURE LABS INC
Category: otc | Type: HUMAN OTC DRUG LABEL
Date: 20171218

ACTIVE INGREDIENTS: ZINC OXIDE 120 mg/1 mL
INACTIVE INGREDIENTS: WATER; CAPRYLIC/CAPRIC/LAURIC TRIGLYCERIDE; POLYGLYCERYL-2 SESQUIISOSTEARATE; CETYL OCTACOSANOATE; POLYSORBATE 60; PEG-20 SORBITAN STEARATE; PHENOXYETHANOL; HYALURONATE SODIUM; CAPRYLYL GLYCOL; HEXYLENE GLYCOL; YEAST MANNAN; STEARYL ALCOHOL; POLYHYDROXYSTEARIC ACID (2300 MW); ISOSTEARIC ACID; POLYGLYCERYL-3 RICINOLEATE; ETHYLHEXYLGLYCERIN; LECITHIN, SOYBEAN; BIOSACCHARIDE GUM-1; CAMELLIA SINENSIS FLOWER; SHEA BUTTER; MALUS DOMESTICA FLOWER; XANTHAN GUM; GLYCERIN; MAGNESIUM SULFATE ANHYDROUS; TOCOPHERYL NICOTINATE, D-.ALPHA.; ALLANTOIN; MAGNESIUM STEARATE; ALUMINUM STEARATE; COPERNICIA ALBA WHOLE; OENOTHERA BIENNIS; RESORCINOL

Drug Facts

Active Ingredients:

Zinc Oxide - 18.9%

Purpose: Sunscreen

INDICATIONS AND USAGE

Uses: Helps prevent sunburn. If used as directed with other sun protection measures (see Direction), decreases the risk of skin cancer and early skin aging caused by the sun.

WARNINGS

For external use only.

Do not use on damaged or broken skin.

WHEN USING

Keep out of eyes. Rinse with water to remove.

Stop use and ask a doctor if rash occurs.

KEEP OUT OF REACH OF CHILDREN

If product is swallowed, get medical help or contact a Poison Control Center right away.

Directions:

- Apply liberally 15 minutes prior to sun exposure.
- Reapply: after 80 minutes of swimming or sweating. Immediately after towel drying. At least every 2 hours.
- Sun Protection Measures. Spending time in the sun increases your risk of skin cancer and early skin aging. To decrease the risk, regularly use a sunscreen with a broad spectrum SPF of 15 or higher and other sun protection measures including:
- limit time in sun sun, especially from 10 am - 2 pm.
- wear long-sleeve shirts, pants, hats and sunglasses.
- Children under 6 months: Ask a doctor.

INACTIVE INGREDIENT

Water, Caprilic/Capric Triglyceride, Polyglyceryl-2 Sesquiisostearate, Cetyl Octanoate, Cera Alba Beeswax, Sodium Hyaluronate, Caprylyl Glycol, Hexylene Glycol, Yeast Extract, Biosaccharide Gum-1, Camellia Sinensis Leaf Extract, Butyrospermum Parkii (Shea butter/Vit. A,E,F), Malus Domestica Fruit Cell Culture, Xanthan Gum, Glycerin, Lecithin, Xanthan Gum, Magnesium Sulfate, Tocopheryl Acetate, Allantoin, Magnesium Stearate, Aluminum Stearate, Isostearic Acid, Polyhydroxystearic Acid, Polyglyceryl-3 Ricinoleate, Phenoxyethanol, Ethylhexylglycerin, Copemicia Cerifera Wax, Oenothera Biennis Oil, Resorcinol.

OTHER SAFETY INFORMATION

Protect this product from excessive heat and direct sun.

QUESTIONS

Call toll free 1-800 830-1491 in the USA.

info@atzen.com

PACKAGE LABEL

Toll free in USA: 800.830.1491

Email: info@atzen.com

www.atzen.com

Developed in France. Made in USA.